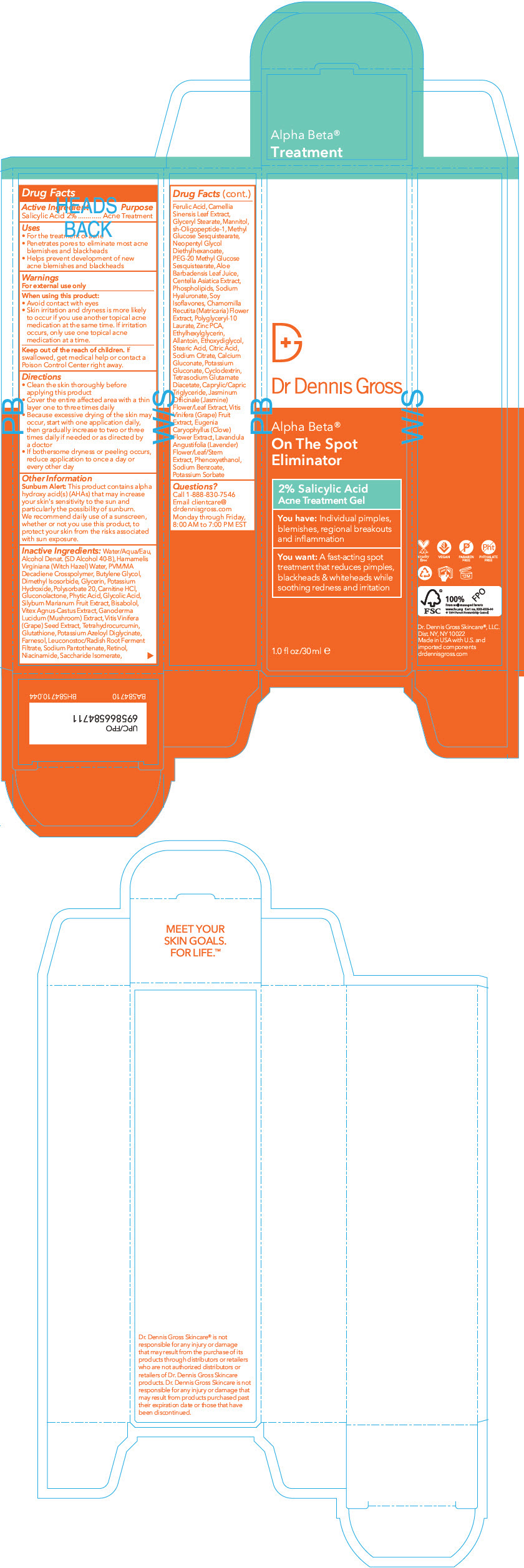 DRUG LABEL: Dr. Dennis Gross Alpha Beta On the Spot Eliminator
NDC: 51326-057 | Form: GEL
Manufacturer: Topiderm, Inc
Category: otc | Type: HUMAN OTC DRUG LABEL
Date: 20231116

ACTIVE INGREDIENTS: SALICYLIC ACID 20 mg/1 mL
INACTIVE INGREDIENTS: WATER; ALCOHOL; HAMAMELIS VIRGINIANA LEAF WATER; BUTYLENE GLYCOL; DIMETHYL ISOSORBIDE; GLYCERIN; POTASSIUM HYDROXYCITRATE; POLYSORBATE 20; CARNITINE HYDROCHLORIDE, (+)-; GLUCONOLACTONE; FYTIC ACID; GLYCOLIC ACID; SILYBUM MARIANUM WHOLE; .ALPHA.-BISABOLOL, (+)-; VITEX AGNUS-CASTUS LEAF; REISHI; TETRAHYDRODIFERULOYLMETHANE; GLUTATHIONE; POTASSIUM AZELOYL DIGLYCINATE; FARNESOL; LEUCONOSTOC/RADISH ROOT FERMENT FILTRATE; SODIUM PANTOTHENATE; RETINOL; NIACINAMIDE; SACCHARIDE ISOMERATE; FERULIC ACID; GREEN TEA LEAF; GLYCERYL MONOSTEARATE; MANNITOL; NEPIDERMIN; METHYL GLUCOSE SESQUISTEARATE; ALOE VERA LEAF; CENTELLA ASIATICA LEAF; HYALURONATE SODIUM; GENISTEIN; MATRICARIA CHAMOMILLA LEAF; POLYGLYCERYL-10 LAURATE; ZINC PIDOLATE; ETHYLHEXYLGLYCERIN; ALLANTOIN; DIETHYLENE GLYCOL MONOETHYL ETHER; STEARIC ACID; CITRIC ACID MONOHYDRATE; SODIUM CITRATE, UNSPECIFIED FORM; CALCIUM GLUCONATE; POTASSIUM GLUCONATE; CYCLODEXTRINS; TETRASODIUM GLUTAMATE DIACETATE; MEDIUM-CHAIN TRIGLYCERIDES; JASMINUM OFFICINALE FLOWER; VITIS VINIFERA FRUIT OIL; CLOVE LEAF OIL; PHENOXYETHANOL; SODIUM BENZOATE; POTASSIUM SORBATE

Alpha Beta® On The Spot Eliminator

Drug Facts

Active Ingredient

Salicylic Acid 2%

Purpose

Acne Treatment

Uses

- For the treatment of acne
- Penetrates pores to eliminate most acne blemishes and blackheads
- Helps prevent development of new acne blemishes and blackheads

Warnings

For external use only

When using this product

- Avoid contact with eyes
- Skin irritation and dryness is more likely to occur if you use another topical acne medication at the same time. If irritation occurs, only use one topical acne medication at a time.

Keep out of reach of children. If swallowed, get medical help or contact a Poison Control Center right away.

Directions

- Clean the skin thoroughly before applying this product.
- Cover the entire affected area with a thin layer one to three times daily.
- Because excessive drying of the skin may occur, start with one application daily, then gradually increase to two or three times daily if needed or as directed by a doctor
- If bothersome dryness or peeling occur, reduce application to once a day or every other day

Other Information

Sunburn alert

This product contains alpha hydroxy acid(s) (AHAs) that may increase your skin's sensitivity to the sun and particularly the possibility of sunburn. We recommend daily use of a sunscreen, whether or not you use this product, to protect your skin from the risks associated with sun exposure.

Inactive ingredients

Water/Aqua/Eau, Alcohol Denat. (SD Alcohol 40-B), Hamamelis Virginiana (Witch Hazel) Water, PVM/MA Decadiene Crosspolymer, Butylene Glycol, Dimethyl Isosorbide, Glycerin, Potassium Hydroxide, Polysorbate 20, Carnitine HCl, Gluconolactone, Phytic Acid, Glycolic Acid, Silybum Marianum Fruit Extract, Bisabolol, Vitex Agnus-Castus Extract, Ganoderma Lucidum (Mushroom) Extract, Vitis Vinifera (Grape) Seed Extract, Tetrahydrocurcumin, Glutathione, Potassium Azeloyl Diglycinate, Farnesol, Leuconostoc/Radish Root Ferment Filtrate, Sodium Pantothenate, Retinol, Niacinamide, Saccharide Isomerate, Ferulic Acid, Camellia Sinensis Leaf Extract, Glyceryl Stearate, Mannitol, sh-Oligopeptide-1, Methyl Glucose Sesquistearate, Neopentyl Glycol Diethylhexanoate, PEG-20 Methyl Glucose Sesquistearate, Aloe Barbadensis Leaf Juice, Centella Asiatica Extract, Phospholipids, Sodium Hyaluronate, Soy Isoflavones, Chamomilla Recutita (Matricaria) Flower Extract, Polyglyceryl-10 Laurate, Zinc PCA, Ethylhexylglycerin, Allantoin, Ethoxydiglycol, Stearic Acid, Citric Acid, Sodium Citrate, Calcium Gluconate, Potassium Gluconate, Cyclodextrin, Tetrasodium Glutamate Diacetate, Caprylic/Capric Triglyceride, Jasminum Officinale (Jasmine) Flower/Leaf Extract, Vitis Vinifera (Grape) Fruit Extract, Eugenia Caryophyllus (Clove) Flower Extract, Lavandula Angustifolia (Lavender) Flower/Leaf/Stem Extract, Phenoxyethanol, Sodium Benzoate, Potassium Sorbate

Questions?

Call 1-888-830-7546

Email clientcare@drdennisgross.com

Monday through Friday, 8:00 AM to 7:00 PM EST

PRINCIPAL DISPLAY PANEL - 30 ml Tube Box

Dr Dennis Gross

Alpha Beta®
On The Spot
Eliminator

2% Salicylic Acid
Acne Treatment Gel

You have: Individual pimples,
blemishes, regional breakouts
and inflammation

You want: A fast-acting spot
treatment that reduces pimples,
blackheads & whiteheads while
soothing redness and irritation

1.0 fl oz/30 ml ℮